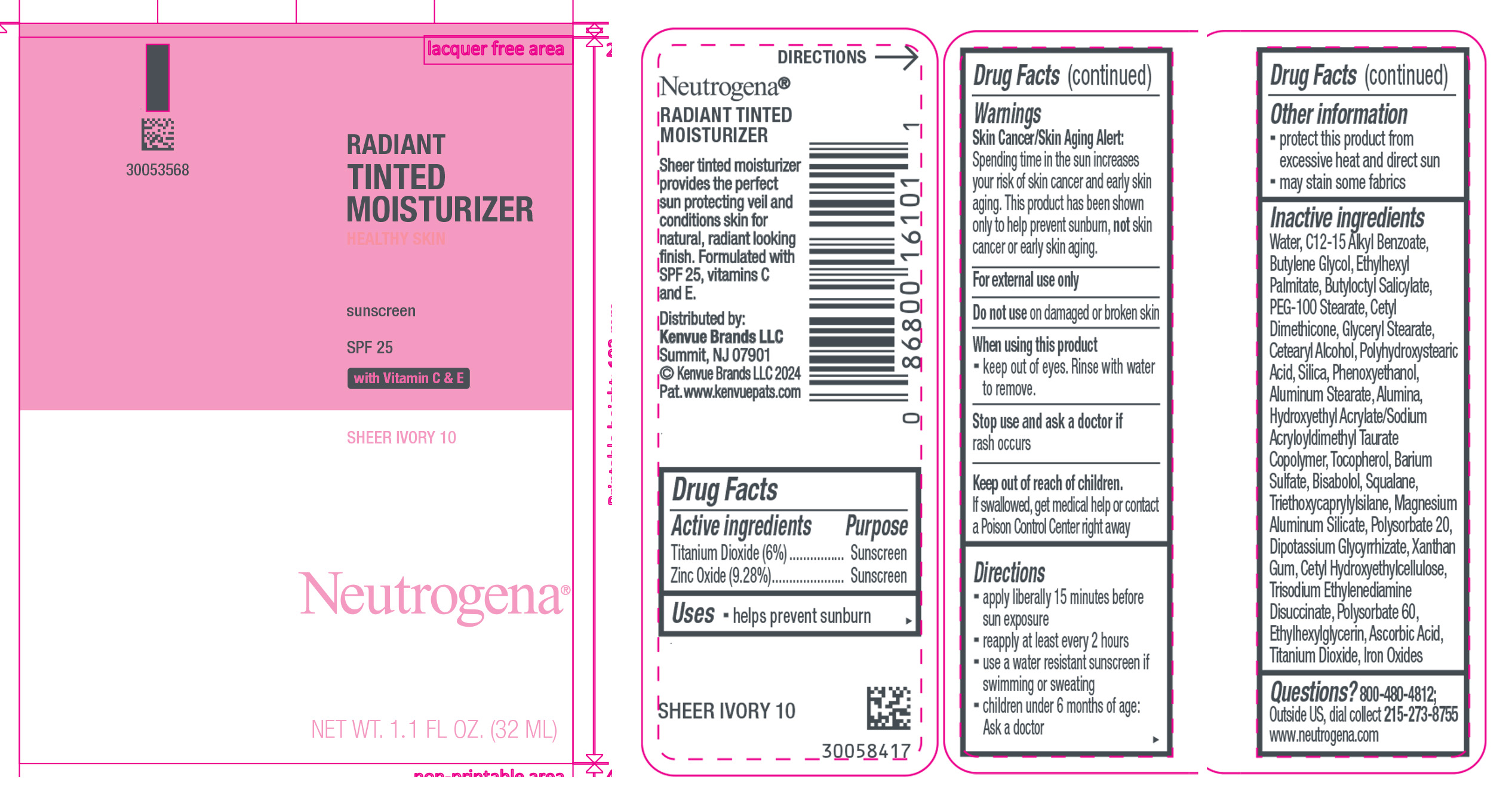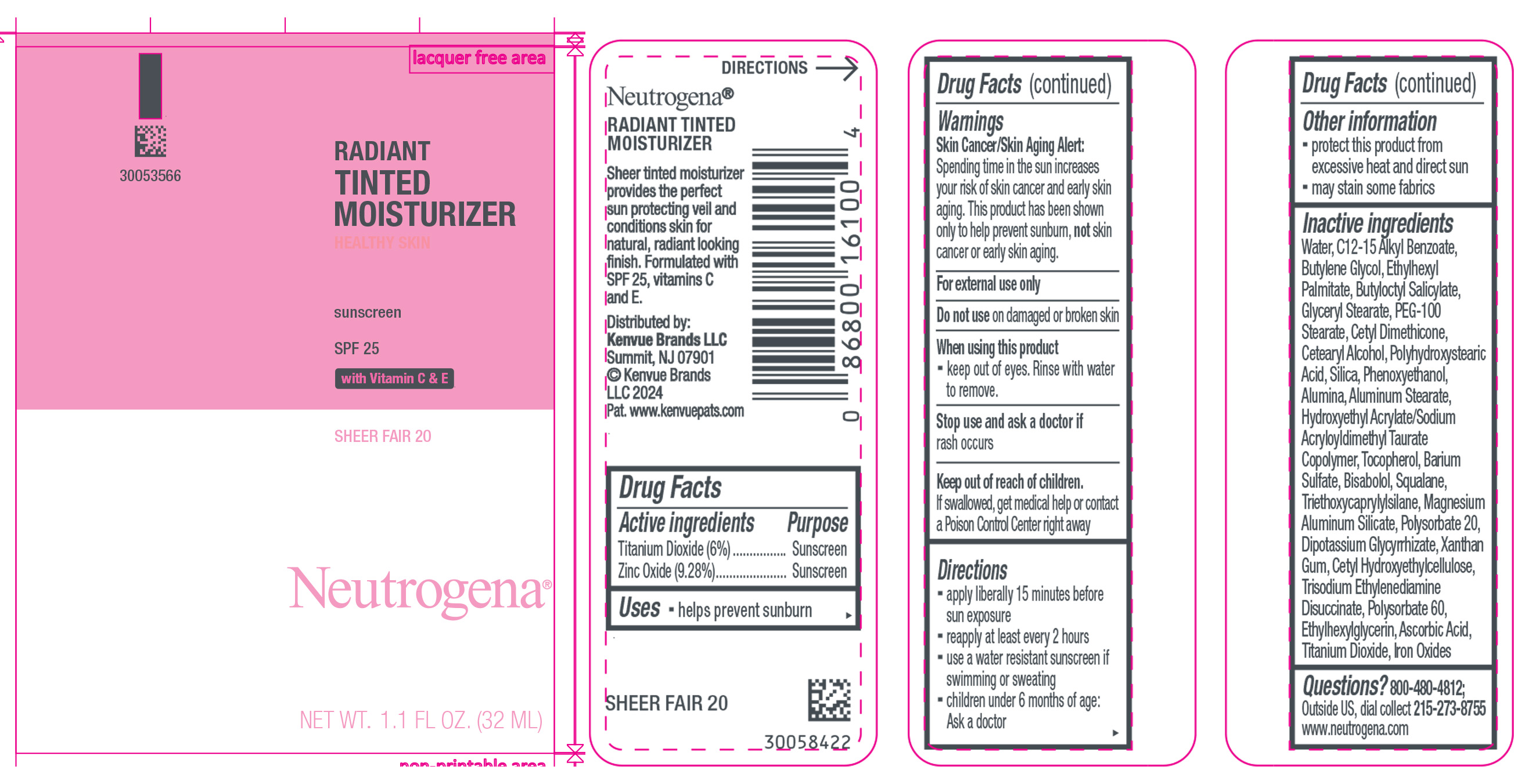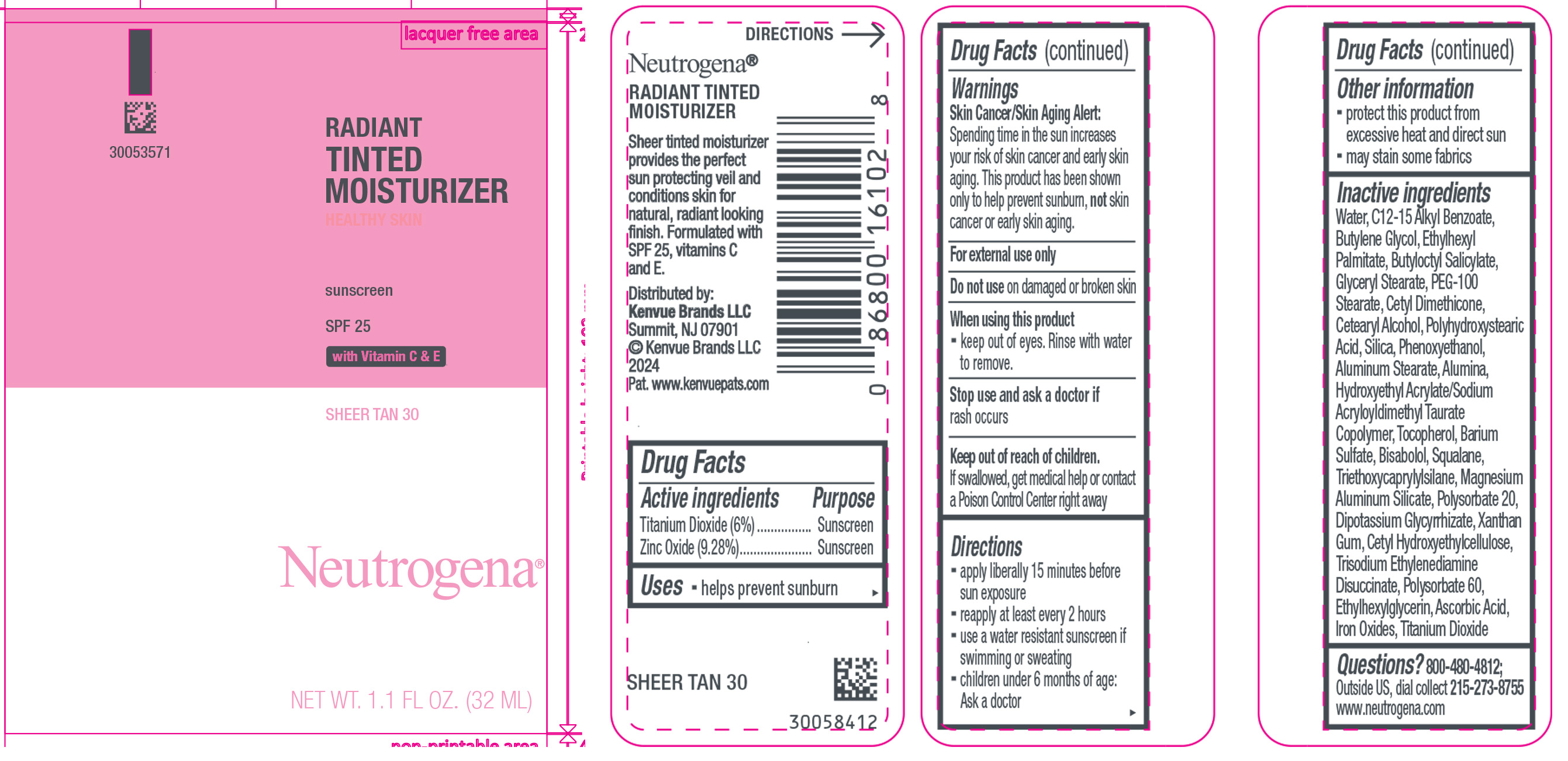 DRUG LABEL: Neutrogena Healthy Skin Radiant Tinted Moisturizer Sunscreen Broad Spectrum SPF 25, Sheer Ivory 10
NDC: 69968-0830 | Form: LOTION
Manufacturer: Kenvue Brands LLC
Category: otc | Type: HUMAN OTC DRUG LABEL
Date: 20241212

ACTIVE INGREDIENTS: ZINC OXIDE 92.8 mg/1 mL; TITANIUM DIOXIDE 60 mg/1 mL
INACTIVE INGREDIENTS: WATER; TOCOPHEROL; POLYSORBATE 20; ETHYLHEXYLGLYCERIN; CETYL DIMETHICONE/BIS-VINYLDIMETHICONE CROSSPOLYMER; HYDROXYETHYL ACRYLATE/SODIUM ACRYLOYLDIMETHYL TAURATE COPOLYMER (45000 MPA.S AT 1%); TRIETHOXYCAPRYLYLSILANE; TRISODIUM ETHYLENEDIAMINE DISUCCINATE; ALKYL (C12-15) BENZOATE; ETHYLHEXYL PALMITATE; PEG-100 STEARATE; BARIUM SULFATE; MAGNESIUM ALUMINUM SILICATE; ASCORBIC ACID; FERRIC OXIDE RED; SQUALANE; CETOSTEARYL ALCOHOL; GLYCYRRHIZINATE DIPOTASSIUM; BUTYLENE GLYCOL; GLYCERYL MONOSTEARATE; SILICON DIOXIDE; PHENOXYETHANOL; BUTYLOCTYL SALICYLATE; ALUMINUM STEARATE; ALUMINUM OXIDE; LEVOMENOL; XANTHAN GUM; POLYSORBATE 60

Neutrogena Healthy Skin Radiant Tinted Moisturizer Sunscreen Broad Spectrum SPF 25, Sheer Ivory 10
Neutrogena Healthy Skin Radiant Tinted Moisturizer Sunscreen Broad Spectrum SPF 25, Sheer Fair 20
Neutrogena Healthy Skin Radiant Tinted Moisturizer Sunscreen Broad Spectrum SPF 25, Sheer Tan 30

Drug Facts

ACTIVE INGREDIENT

Active ingredients | Purpose
Titanium Dioxide (6%) | Sunscreen
Zinc Oxide (9.28%) | Sunscreen

Uses

- helps prevent sunburn

Warnings

Skin Cancer/Skin Aging Alert:

Spending time in the sun increases your risk of skin cancer and early skin aging. This product has been shown only to help prevent sunburn, not skin cancer or early skin aging.

For external use only

Do not use on damaged or broken skin

When using this product

- keep out of eyes. Rinse with water to remove.

Stop use and ask a doctor if rash occurs

Keep out of reach of children.

If swallowed, get medical help or contact a Poison Control Center right away

Directions

- apply liberally 15 minutes before sun exposure
- reapply at least every 2 hours
- use a water resistant sunscreen if swimming or sweating
- children under 6 months of age: Ask a doctor

Other Information

- protect this product from excessive heat and direct sun
- may stain some fabrics

Inactive ingredients

Water, C12-15 Alkyl Benzoate, Butylene Glycol, Ethylhexyl Palmitate, Butyloctyl Salicylate, Glyceryl Stearate, PEG-100 Stearate, Cetyl Dimethicone, Cetearyl Alcohol, Polyhydroxystearic Acid, Silica, Phenoxyethanol, Alumina, Aluminum Stearate, Hydroxyethyl Acrylate/Sodium Acryloyldimethyl Taurate Copolymer, Tocopherol, Barium Sulfate, Bisabolol, Squalane, Triethoxycaprylylsilane, Magnesium Aluminum Silicate, Polysorbate 20, Dipotassium Glycyrrhizate, Xanthan Gum, Cetyl Hydroxyethylcellulose, Trisodium Ethylenediamine Disuccinate, Polysorbate 60, Ethylhexylglycerin, Ascorbic Acid, Titanium Dioxide, Iron Oxides

Questions?

800-480-4812; Outside US, dial collect 215-273-8755 www.neutrogena.com

Distributed by:
Kenvue Brands LLC
Summit, NJ 07901

PRINCIPAL DISPLAY PANEL - 32 mL Tube Label - sheer ivory 10

RADIANT

TINTED

MOISTURIZER

HEALTHY SKIN

sunscreen

SPF 25

with Vitamin C & E

SHEER IVORY 10

Neutrogena®

NET WT. 1.1 FL OZ. (32ML)

PRINCIPAL DISPLAY PANEL - 32 mL Tube Label - sheer fair 20

RADIANT

TINTED

MOISTURIZER

HEALTHY SKIN

sunscreen

SPF 25

with Vitamin C & E

SHEER FAIR 20

Neutrogena®

NET WT. 1.1 FL OZ. (32ML)

PRINCIPAL DISPLAY PANEL - 32 mL Tube Label - sheer tan 30

RADIANT

TINTED

MOISTURIZER

HEALTHY SKIN

sunscreen

SPF 25

with Vitamin C & E

SHEER TAN 30

Neutrogena®

NET WT. 1.1 FL OZ. (32ML)